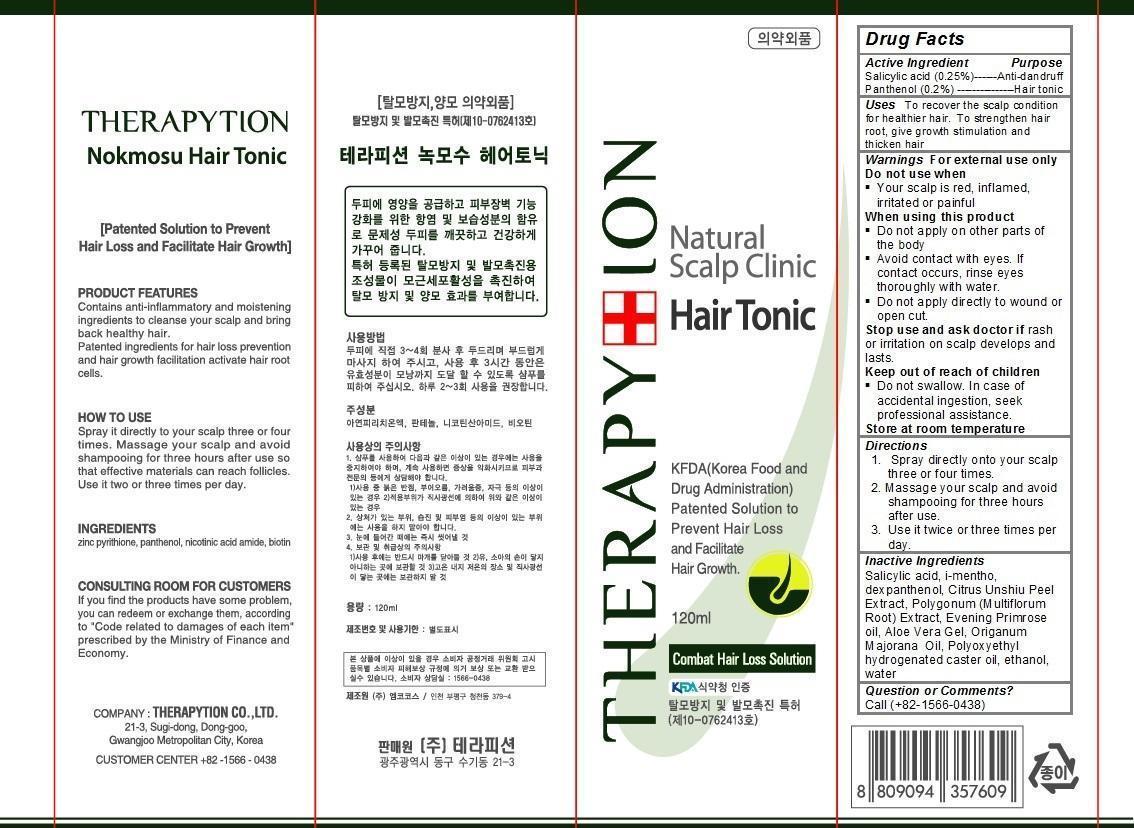 DRUG LABEL: Therapytion Nokmosu Hair Tonic
NDC: 63214-100 | Form: SPRAY
Manufacturer: Therapytion Co., Ltd.
Category: otc | Type: HUMAN OTC DRUG LABEL
Date: 20140422

ACTIVE INGREDIENTS: SALICYLIC ACID 0.3 g/120 g; PANTHENOL 0.24 g/120 g
INACTIVE INGREDIENTS: MENTHOL; DEXPANTHENOL; TANGERINE PEEL; POLYGONUM ARENASTRUM WHOLE; EVENING PRIMROSE OIL; ALOE VERA WHOLE; ORIGANUM MAJORANA WHOLE; CASTOR OIL; ALCOHOL; water

Therapytion Nokmosu Hair Tonic